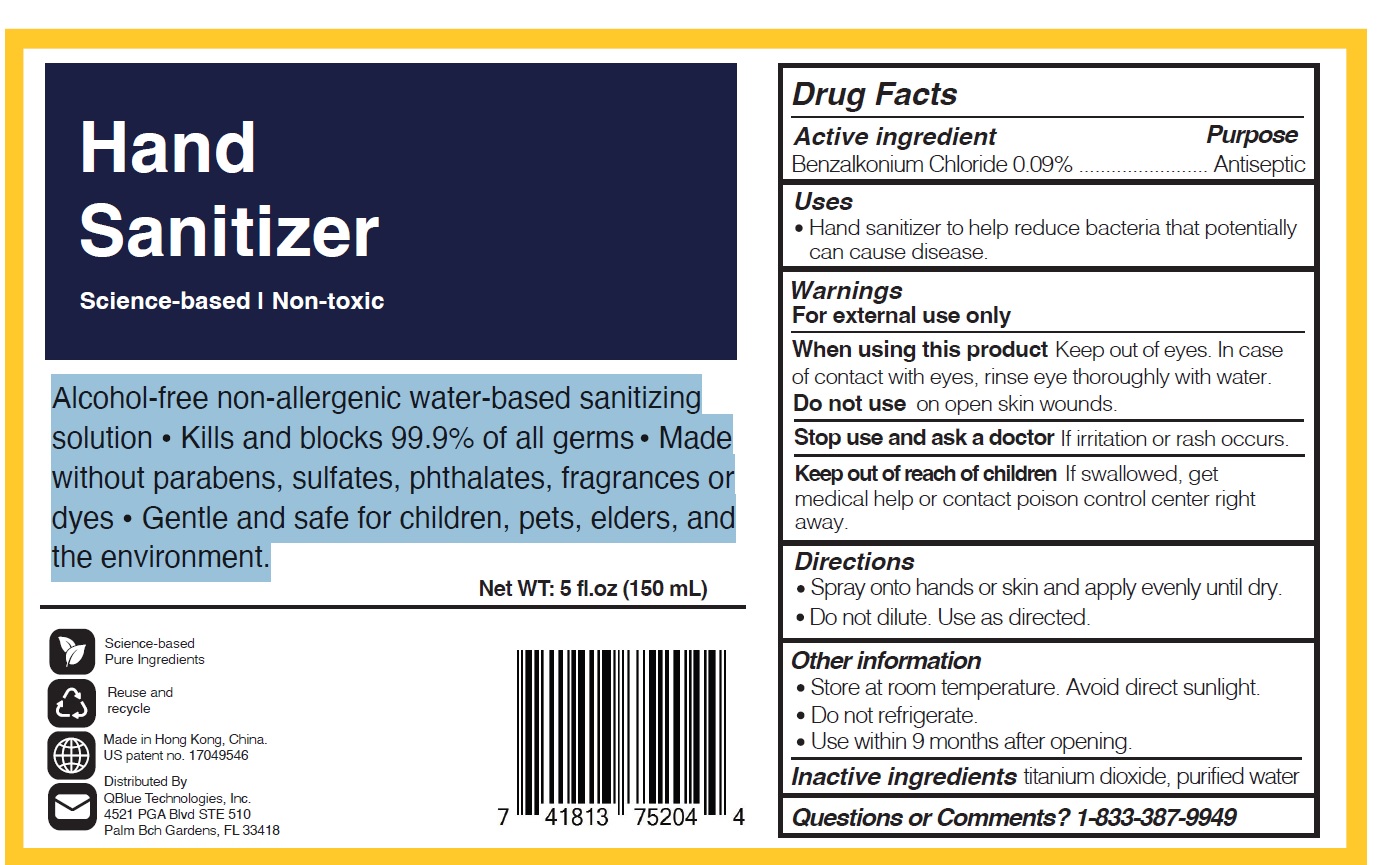 DRUG LABEL: HAND SANITIZER
NDC: 83388-001 | Form: SOLUTION
Manufacturer: QBLUE TECHNOLOGIES, INC.
Category: otc | Type: HUMAN OTC DRUG LABEL
Date: 20230410

ACTIVE INGREDIENTS: BENZALKONIUM CHLORIDE 0.9 mg/1 mL
INACTIVE INGREDIENTS: TITANIUM DIOXIDE; WATER

QBlue Hand Sanitizer Solution 150mL (83388-001-15)

Drug Facts - Active Ingredient

Benzalkonium Chloride 0.09%

Purpose

Antiseptic

Uses

Hand sanitizer to help reduce bacteria that potentially can cause disease.

Warnings

For external use only.

When using this product

Keep out of eyes. In case of contact with eyes, rinse eye thoroughly with water.

Do not Use

on open skin wounds.

Stop Use and ask a doctor

if irritation or rash occurs.

Keep out of reach of children.

If swallowed, get medical help or contact poison control center right away.

Directions

- Spray onto hands or skin and apply evenly until dry.
- Do not dilute. Use as directed.

Other Information

- Store at room temperature. Avoid direct sunlight.
- Do not refrigerate.
- Use within 9 months after opening

Inactive Ingredients

titanium dioxide, purified water

Questions or comment?

1-833-387-9949

PDP

NDC: 83388-001-15

Alcohol-free non-allergenic water-based sanitizing solution. Kills and blocks 99.9% of all germs. Made without parabens, sulfates, phthalates, fragrances or dyes. Gentle and safe for children, pets, elders, and the environment.

Science-based
Pure Ingredients
Net WT: 5 fl.oz (150 mL)
Reuse and
recycle
Made in Hong Kong, China.
US patent no. 17049546
Distributed By
QBlue Technologies, Inc.
4521 PGA Blvd STE 510
Palm Bch Gardens, FL 33418